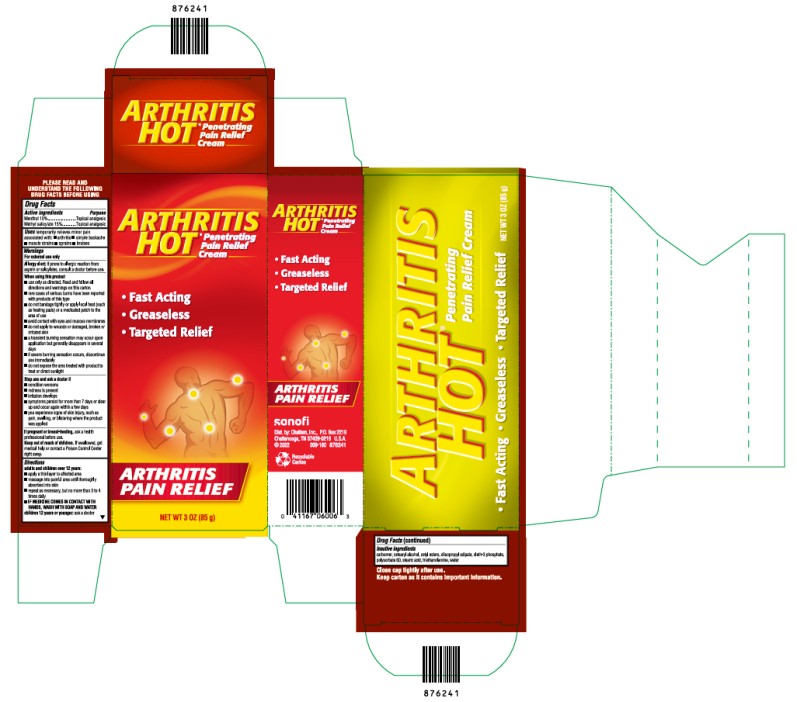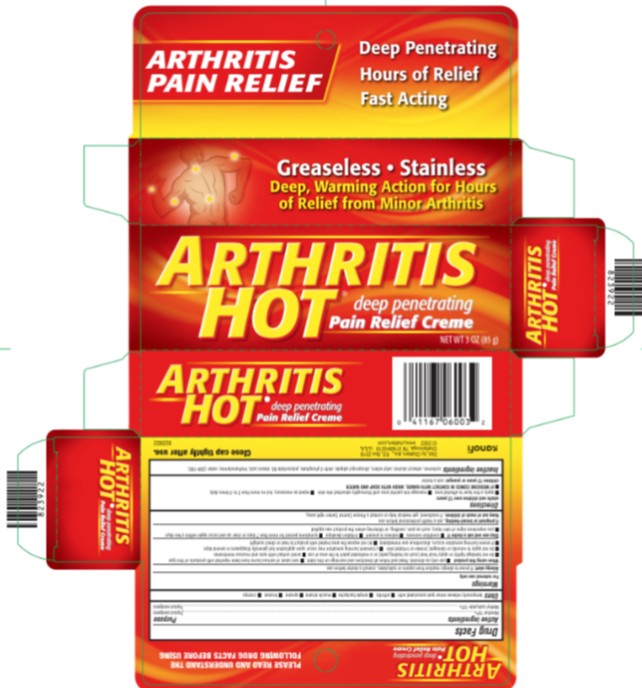 DRUG LABEL: Arthritis Hot
NDC: 41167-0600 | Form: CREAM
Manufacturer: Chattem, Inc.
Category: otc | Type: HUMAN OTC DRUG LABEL
Date: 20250113

ACTIVE INGREDIENTS: MENTHOL 10 g/100 g; METHYL SALICYLATE 15 g/100 g
INACTIVE INGREDIENTS: CETYL ESTERS WAX; DIISOPROPYL ADIPATE; OLETH-3 PHOSPHATE; STEARIC ACID; WATER; CARBOMER HOMOPOLYMER, UNSPECIFIED TYPE; TROLAMINE; CETEARYL ALCOHOL; POLYSORBATE 60

Arthritis Hot

Drug Facts

Active ingredients

Menthol 10%

Methyl salicylate 15%

Purpose

Topical analgesic

Uses

temporarily relieves minor pain associated with:

- arthritis
- simple backache
- muscle strains
- sprains
- bruises
- cramps

Warnings

For external use only

Allergy alert: If prone to allergic reaction from aspirin or salicylates, consult a doctor before use.

When using this product

■ use only as directed. Read and follow all directions and warnings on this label.

■ rare cases of serious burns have been reported with products of this type

■ do not bandage tightly or apply local heat (such as heating pads) or a medicated patch to the area of use

■ avoid contact with eyes and mucous membranes

■ do not apply to wounds or damaged, broken or irritated skin

■ a transient burning sensation may occur upon application but generally disappears in several days

■ if severe burning sensation occurs, discontinue use immediately

■ do not expose the area treated with product to heat or direct sunlight

Stop use and ask a doctor if

- condition worsens
- redness is present
- Irritation develops
- symptoms persist for more than 7 days or clear up and occur again within a few days
- you experience signs of skin injury, such as pain, swelling, or blistering where the product was applied

If pregnant or breast-feeding,

ask a health care professional before use.

Keep out of reach of children.

If swallowed, get medical help or contact a Poison Control Center right away.

Directions

adults and children over 12 years:

■ apply a thin layer to affected area

■ massage into painful area until thoroughly absorbed into skin

■ repeat as necessary, but no more than 3 to 4 times daily

■ IF MEDICINE COMES IN CONTACT WITH HANDS, WASH WITH SOAP AND WATER

children 12 years or younger: ask a doctor

Inactive ingredients

Carbomer, cetearyl alcohol, cetyl esters, diisapropyl adipate, oleth-3 phosphate, polysorbate 60, stearic acid, triethanolamine, water

Arthritis Hot Cream

Active ingredients

Menthol 10%

Methyl salicylate 15%

Purpose

Topical analgesic

Uses

temporarily relieves minor pain associated with:

- arthritis
- simple backache
- muscle strains
- sprains
- bruises

Warnings

For external use only

Allergy alert: if prone to allergic reaction from aspirin or salicylates, consult a doctor before use.

When using this product

■ use only as directed. Read and follow all directions and warnings on this label.

■ rare cases of serious burns have been reported with products of this type

■ do not bandage tightly or apply local heat (such as heating pads) or a medicated patch to the area of use

■ avoid contact with eyes and mucous membranes

■ do not apply to wounds or damaged, broken or irritated skin

■ a transient burning sensation may occur upon application but generally disappears in several days

■ if severe burning sensation occurs, discontinue use immediately

■ do not expose the area treated with product to heat or direct sunlight

Stop use and ask a doctor if

- condition worsens
- redness is present
- Irritation develops
- symptoms persist for more than 7 days or clear up and occur again within a few days
- you experience signs of skin injury, such as pain, swelling, or blistering where the product was applied

If pregnant or breast-feeding,

ask a health professional before use.

Keep out of reach of children.

If swallowed, get medical help or contact a Poison Control Center right away.

Directions

adults and children over 12 years:

■ apply a thin layer to affected area

■ massage into painful area until thoroughly absorbed into skin

■ repeat as necessary, but no more than 3 to 4 times daily

■ IF MEDICINE COMES IN CONTACT WITH HANDS, WASH WITH SOAP AND WATER

children 12 years or younger: ask a doctor

Inactive ingredients

Carbomer, cetearyl alcohol, cetyl esters, diisapropyl adipate, oleth-3 phosphate, polysorbate 60, stearic acid, triethanolamine, water

PRINCIPAL DISPLAY PANEL

NDC 41167-0600-4
Arthritis Penetrating Pain Relief Cream
NET WT 3 OZ (85g)

PRINCIPAL DISPLAY PANEL

NDC 41167-0600-3
Arthritis Deep Penetrating Pain Relief Crème
NET WT 3 OZ (85g)